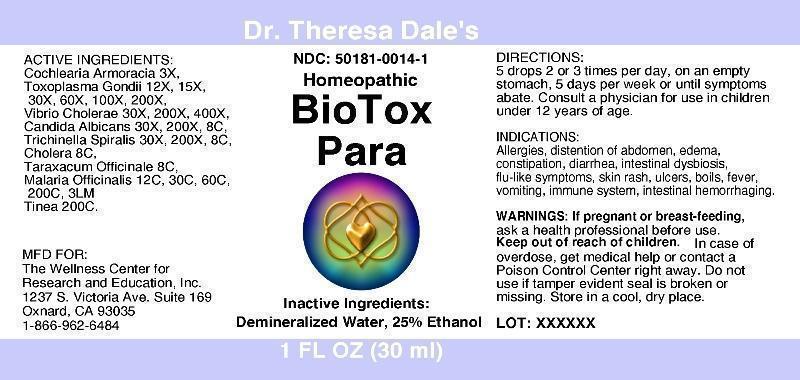 DRUG LABEL: Biotox Para
NDC: 50181-0014 | Form: LIQUID
Manufacturer: The Wellness Center
Category: homeopathic | Type: HUMAN OTC DRUG LABEL
Date: 20250529

ACTIVE INGREDIENTS: HORSERADISH 3 [hp_X]/1 mL; TOXOPLASMA GONDII 12 [hp_X]/1 mL; VIBRIO CHOLERAE 30 [hp_X]/1 mL; CANDIDA ALBICANS 30 [hp_X]/1 mL; TRICHINELLA SPIRALIS 30 [hp_X]/1 mL; TARAXACUM OFFICINALE 8 [hp_C]/1 mL; PLASMODIUM MALARIAE 12 [hp_C]/1 mL; TRICHOPHYTON RUBRUM 200 [hp_C]/1 mL
INACTIVE INGREDIENTS: WATER; ALCOHOL

Drug Facts

ACTIVE INGREDIENTS

Cochlearia Armoracia 3X, Toxoplasma Gondii 12X, 15X, 30X, 60X, 100X, 200X, Vibrio Cholerae 30X, 200X, 400X, Candida Albicans 30X, 200X, 8C, Trichinella Spiralis 30X, 200X, 8C, Cholera 8C, Taraxacum Officinale 8C, Malaria Officinalis 12C, 30C, 60C, 200C, 3LM, Tinea 200C

INDICATIONS

Allergies, distention of abdomen, edema, constipation, diarrhea, intestinal dysbiosis, flu-like symptoms, skin rash, ulcers, boils, fever, vomiting, immune system, intestinal hemorrhaging.

WARNINGS

If pregnant or breast-feeding, ask a health professional before use. Keep out of reach of children. In case of overdose, get medical help or contact a Poison Control Center right away. Do not use if tamper evident seal is broken or missing.

DIRECTIONS

5 drops 2 or 3 times per day, on an empty stomach, 5 days per week or until symptoms abate. Consult a physician for use in children under 12 years of age.

INACTIVE INGREDIENTS

Demineralized Water, 25% Ethanol

KEEP OUT OF REACH OF CHILDREN

In case of overdose, get medical help or contact a Poison Control Center right away.

INDICATIONS AND USAGE

Allergies, distention of abdomen, edema, constipation, diarrhea, intestinal dysbiosis, flu-like symptoms, skin rash, ulcers, boils, fever, vomiting, immune system, intestinal hemorrhaging.

QUESTIONS

MFD FOR:

The Wellness Center for

Research and Education, Inc.

1237 S. Victoria Ave. Suite 169

Oxnard, CA 93035

1-866-962-6484

PACKAGE LABEL

Dr. Theresa Dale's

NDC: 50181-0014-1

Bio Tox

Para

1 FL OZ (30 ml)